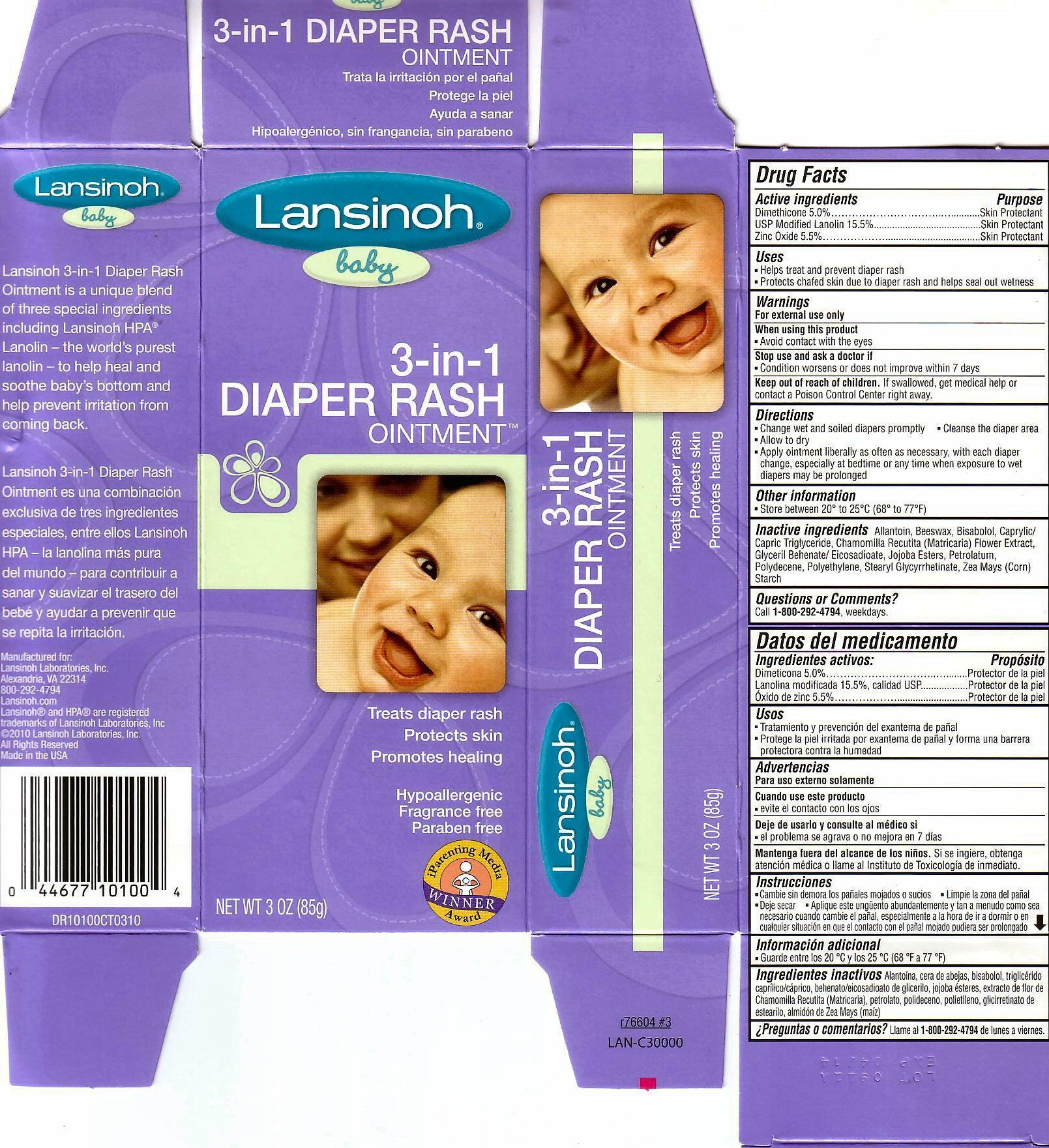 DRUG LABEL: LANSINOH BABY
NDC: 53997-100 | Form: OINTMENT
Manufacturer: Lansinoh Laboratories, Inc.
Category: otc | Type: HUMAN OTC DRUG LABEL
Date: 20111215

ACTIVE INGREDIENTS: DIMETHICONE 4.25 g/85 g; LANOLIN 13.17 g/85 g; ZINC OXIDE 4.675 g/85 g
INACTIVE INGREDIENTS: ALLANTOIN; YELLOW WAX; LEVOMENOL; MEDIUM-CHAIN TRIGLYCERIDES; CHAMOMILE; GLYCERYL BEHENATE; JOJOBA OIL; PETROLATUM; HYDROGENATED POLYDECENE (550 MW); HIGH DENSITY POLYETHYLENE; STEARYL GLYCYRRHETINATE; STARCH, CORN

ACTIVE INGREDIENTS

DRUG FACTS DIMETHICONE 5.0% USP MODIFIED LANOLIN 15.5 % ZINC OXIDE 5.5 %
DATOS DEL MEDICAMENTO DIMETICONA 5.0% LANOLINA MODIFICADA 15.5%, CALIDAD USP OXIDO DE ZINC 5.5%

INACTIVE INGREDIENT

ALLANTOIN, BEESWAX, BISABOLO, CAPRYLIC/CAPRIC TRIGLYCERIDE, CHAMOMILLA RECUTITA (MATRICARIA)FLOWER EXTRACT, GLYCERIL BEHENATE/EICOSADIOATE, JOJOBA ESTERS, PETROLATUM, POLYDECENE, POLYETHYLENE, STEARYL GLYCYRRHETINATE, ZEA MAYS (CORN) STARCH
ALANTOINA, CERA DE ABEJAS, BISBOLOL, TRIGLICERIDO CAPRIILICO/CAPRICO, BEHENATO/EICOSADIOATO DE GLICERILO, JOJOBA ESTERES, EXTRACTO DE FLOR DE CHAMOMILLA RECUTITA (MATRICARIA), PETROLATO, POLIDECENO, POLIETILENO, GLICIRRETINATO DE ESTEARILO, ALMIDON DE ZEA MAYS (MAIZ)

PURPOSE

SKIN PROTECTANT
PROTECTOR DE LA PIEL

WARNINGS

FOR EXTERNAL USE ONLY WHEN USING THIS PRODUCT AVOID CONTACT WITH THE EYES STOP USE AND ASK A DOCTOR IF CONDITION WORSENS OR DOES NOT IMPROVE WITH IN 7 DAYS.
PARA USO EXTERNO SOLAMENTE CUANDO USE ESTE PRODUCTO EVITE EL CONTACTO CON LOS OJOS DEJE DE USARLO Y CONSULTE AL MEDICO SI EL PROBLEMA SE AGRAVA O NO MEJORA EN 7 DIAS

KEEP OUT OF REACH OF CHILDREN. IF SWALLOWED, GET MEDICAL HELP OR CONTACT A POISON CONTROL CENTER RIGHT AWAY.
MANTENGA FUERA DEL ALCANCE DE LOS NINOS SI SE INGIERE, OBTENGA ATENCION MEDICA A LLAME AL INSTITUTO DE TOXICOLOGIA DE IMMEDIATO.

DIRECTIONS

CHANGE WET AND SOILED DIAPERS PROMPTLY CLEANSE THE DIAPER AREA ALLOW TO DRY APPLY OINTMENT LIBERALLY AS OFTEN AS NECESSARY, WITH EACH DIAPER CHANGE, ESPECIALLY AT BEDTIME OR ANY TIME WHEN EXPOSURE TO WET DIAPERS MAY BE PROLONGED
CAMBIE SIN DEMORS LOS PANALES MOJADOS O SUCIOS LIMPIE LA ZONA DEL PANAL DEJE SECAR APLIQUE ESTE UNGENTO ABUNDANTEMENTE Y TAN A MENUDO COMO SEA NECESARIO CUANDO CAMBIE EL PANAL, ESPECIALMENTE A LA HORA DE IR A DORMIR O EN CUALQUIER SITUACION EN QUE EL CONTACTO CON EL PANAL MOJADO PUDIERA SER PROLONGADO

OTHER INFORMATION

STORE BETWEEN 20 DEGREES TO 25 DEGREES C (68 DEGREES TO 77 DEGREES F)
GUARDE ENTRE LOS 20C Y 25 C (68 F A 77 F)

QUESTIONS OR COMMENTS

CALL 1-800-292-4794, WEEKDAYS.
LLAME AL 1-800-292-4794 DE LUNES A VIERNES.

INDICATIONS AND USES

TREATS DIAPER RASH PROTECTS SKIN PROMOTES HEALING
TRATA LA IRRITACION POR EL PANAL PROTEGE LA PIEL AYUDA A SANAR

PACKAGE LABEL PRINCIPAL DISPLAY PANEL

LANSINOH BABY LANSINOH 3-IN- 1 DIAPER RASH OINTMENT IS A UNIQUE BLEND OF THREE SPECIAL INGREDIENTS INCLUDING LANSINOH HPA LANOLIN - THE WORLD'S PUREST LANOLIN - TO HELP HEAL AND SOOTHE BABY'S BOTTOM AND HELP PREVENT IRRITATION FROM COMING BACK.
LANSINOH BABY LANSINOH 3-IN- 1 DIAPER RASH OINTMENT ES UNA COMBINACION EXCLUSIVA DE TRES INGREDIENTES ESPECIALES, ENTRE ELLOS LANSINOH HPA - LA LANOLINA MAS PURA DEL MUNDO - PARA CONTRIBUIR A SANAR Y SUAVIZAR EL PREVENIR QUE SE REPITA LA IRRITACION.
MANUFACTURED FOR: LANSINOH LABORATORIES, INC. ALEXANDRIA, VA 22314 800-292-4794 LANSINOH.COM LANSINOH R AND HPA R ARE REGISTERED TRADEMARKS OF LANSINOH LABORATORIES, INC. C 2010 LANSINOH LABORATORIES, INC. ALL RIGHTS RESERVED MADE IN USA
LANSINOH BABY 3-IN-1 DIAPER RASH OINTMENT TRATA LA IRRITACION POR EL PANAL PROTEG LA PIEL AYUDA A SANAR HIPOALERGENICO, SIN FRAGANCIA, SIN PARABENO
LANSINOH BABY 3-IN-1 DIAPER RASH OINTMENT TREATS DIAPER RASH PROTECTS SKIN PROMOTES HEALING HYPOALLERGENIC FRAGRANCE FREE PARABEN FREE
IPARENTING MEDIA WINNER AWARD
NET WT 3 OZ (85G)